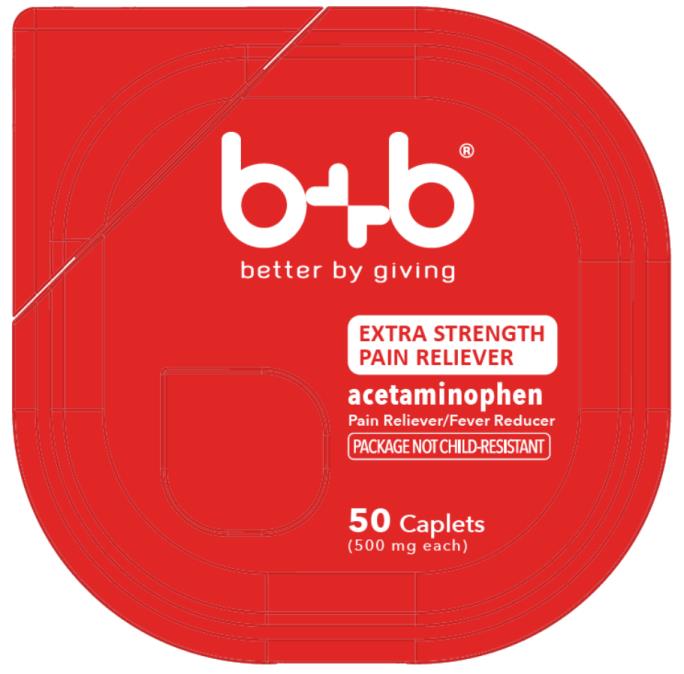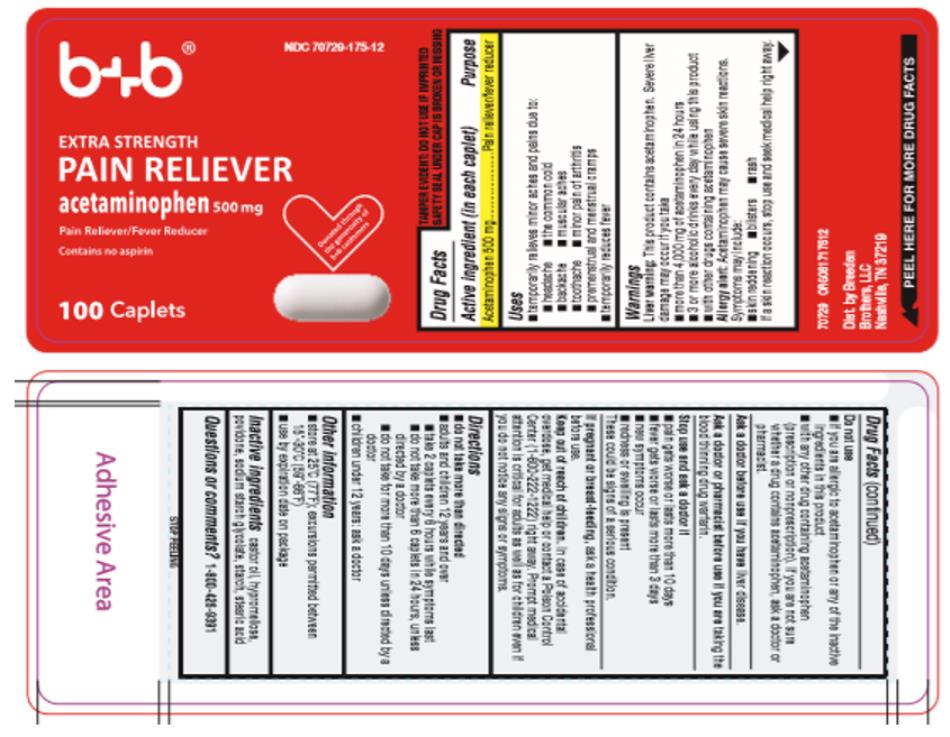 DRUG LABEL: Acetaminophen Caplets
NDC: 70729-001 | Form: TABLET
Manufacturer: Breeden Brothers, LLC
Category: otc | Type: HUMAN OTC DRUG LABEL
Date: 20170215

ACTIVE INGREDIENTS: ACETAMINOPHEN 500 mg/1 1
INACTIVE INGREDIENTS: CASTOR OIL; HYPROMELLOSE, UNSPECIFIED; POVIDONE; STARCH, CORN; SODIUM STARCH GLYCOLATE TYPE A POTATO; STEARIC ACID

Acetaminophen Caplets

Drug Facts

Active ingredient (in each caplet)

Acetaminophen 500 mg

Purpose

Pain reliever/fever reducer

Uses

_ temporarily relieves minor aches and pains due to:
_ headache _ the common cold
_ backache _ minor pain of arthritis
_ toothache _ muscular aches
_ premenstrual and menstrual cramps
_ temporarily reduces fever

Drug Facts (continued)

Warnings

Liver warning: This product contains acetaminophen. Severe

liver damage may occur if you take

_ more than 4,000 mg of acetaminophen in 24 hours

_ with other drugs containing acetaminophen

_ 3 or more alcoholic drinks every day while using this product

Allergy alert: Acetaminophen may cause severe skin reactions.

Symptoms may include: _ rash _ blisters

_ skin reddening If a skin reaction occurs, stop use and seek medical help right away.

Do not use

_ if you are allergic to acetaminophen or any of the inactive ingredients in this product

_ with any other drug containing acetaminophen (prescription or nonprescription). If you are not sure whether a drug

Drug Facts (continued)

contains acetaminophen, ask a doctor or pharmacist.

Ask a doctor before use

if you have liver disease.

Ask a doctor or pharmacist before use

if you are taking the blood thinning drug warfarin.

Stop use and ask a doctor if

_ pain gets worse or lasts more than 10 days

_ fever gets worse or lasts more than 3 days

_ new symptoms occur

_ redness or swelling is present

These could be signs of a serious condition.

If pregnant or breast-feeding,

ask a health professional before use.

Keep out of reach of children.

In case of accidental overdose, get medical help or contact a Poison Control Center (1-800-222-1222) right away. Prompt medical attention is

Drug Facts (continued)

critical for adults as well as for children even if you do not notice any signs or symptoms.

Directions

_ do not take more than directed

_ adults and children 12 years and over

_ take 2 caplets every 6 hours while symptoms last

_ do not take more than 6 caplets in 24 hours, unless directed by a doctor

_ do not take for more than 10 days unless directed by a doctor

_ children under 12 years: ask a doctor

Other information

_ store at 25°C (77°F); excursions permitted between 15°-30°C (59°-86°F)

_ use by expiration date on package

Drug Facts (continued)

Inactive ingredients

castor oil, hypromellose, povidone, sodium starch glycolate, starch, stearic acid

Questions or comments?

1-800-901-2420

Dist. by Breeden Brothers, LLC
Nashville, TN 37219

PRINCIPAL DISPLAY PANEL

b+b
better by giving
EXTRA STRENGTH
PAIN RELIEVER
acetaminophen
Pain Reliever/Fever Reducer
50 Caplets
(500 mg each)

PRINCIPAL DISPLAY PANEL

b+b
NDC 70729-175-12
EXTRA STRENGTH
PAIN RELIEVER
acetaminophen 500 mg
Pain Reliever/Fever Reducer
100 Caplets